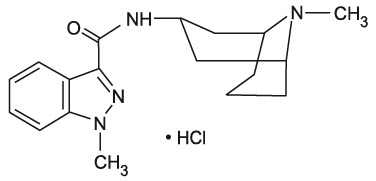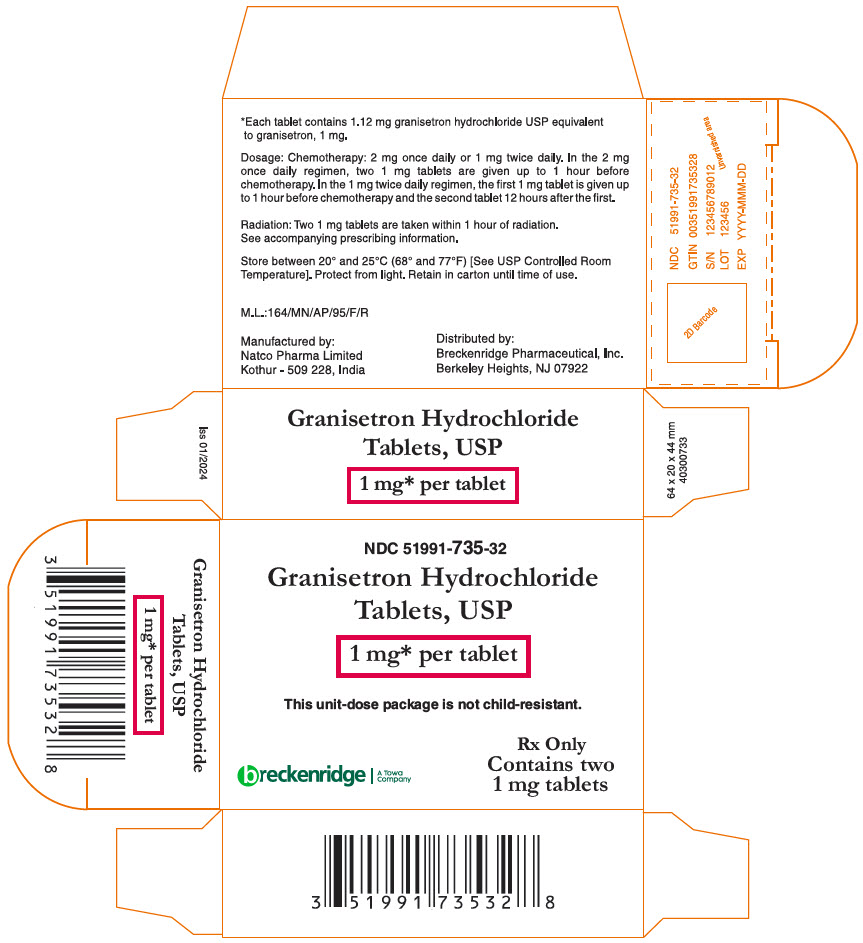 DRUG LABEL: Granisetron Hydrochloride
NDC: 51991-735 | Form: TABLET
Manufacturer: Breckenridge Pharmaceutical, Inc.
Category: prescription | Type: HUMAN PRESCRIPTION DRUG LABEL
Date: 20240229

ACTIVE INGREDIENTS: GRANISETRON HYDROCHLORIDE 1 mg/1 1
INACTIVE INGREDIENTS: MICROCRYSTALLINE CELLULOSE; HYPROMELLOSE, UNSPECIFIED; LACTOSE MONOHYDRATE; MAGNESIUM STEARATE; POLYETHYLENE GLYCOL 4000; POLYSORBATE 80; SODIUM STARCH GLYCOLATE TYPE A POTATO; TITANIUM DIOXIDE

GRANISETRON HYDROCHLORIDE TABLETS, USP

Rx Only

DESCRIPTION

Granisetron hydrochloride tablets USP contain granisetron hydrochloride USP, an antinauseant and antiemetic agent. Chemically it is endo-N-(9-methyl-9-azabicyclo [3.3.1] non-3-yl)-1-methyl-1H-indazole-3-carboxamide hydrochloride.

C18H24N4O∙HCl M.W. 348.9 (312.4 free base)

Granisetron hydrochloride is a white to off-white crystalline powder that is freely soluble in water and slightly soluble in methanol.

Tablets for Oral Administration

Each white, triangular, biconvex, film-coated granisetron hydrochloride tablet USP contains 1.12 mg granisetron hydrochloride equivalent to granisetron, 1 mg. Inactive ingredients are: hypromellose, lactose monohydrate, magnesium stearate, microcrystalline cellulose, polyethylene glycol, polysorbate 80, sodium starch glycolate, and titanium dioxide.

CLINICAL PHARMACOLOGY

Granisetron is a selective 5-hydroxytryptamine3 (5-HT3) receptor antagonist with little or no affinity for other serotonin receptors, including 5-HT1; 5-HT1A; 5-HT1B/C; 5-HT2; for alpha1-, alpha2-, or beta-adrenoreceptors; for dopamine-D2; or for histamine-H1; benzodiazepine; picrotoxin or opioid receptors.

Serotonin receptors of the 5-HT3 type are located peripherally on vagal nerve terminals and centrally in the chemoreceptor trigger zone of the area postrema. During chemotherapy that induces vomiting, mucosal enterochromaffin cells release serotonin, which stimulates 5-HT3 receptors. This evokes vagal afferent discharge, inducing vomiting. Animal studies demonstrate that, in binding to 5-HT3 receptors, granisetron blocks serotonin stimulation and subsequent vomiting after emetogenic stimuli such as cisplatin. In the ferret animal model, a single granisetron injection prevented vomiting due to high-dose cisplatin or arrested vomiting within 5 to 30 seconds.

In most human studies, granisetron has had little effect on blood pressure, heart rate or ECG. No evidence of an effect on plasma prolactin or aldosterone concentrations has been found in other studies.

Following single and multiple oral doses, granisetron hydrochloride tablets slowed colonic transit in normal volunteers. However, granisetron hydrochloride had no effect on oro-cecal transit time in normal volunteers when given as a single intravenous (IV) infusion of 50 mcg/kg or 200 mcg/kg.

Pharmacokinetics

In healthy volunteers and adult cancer patients undergoing chemotherapy, administration of granisetron hydrochloride tablets produced mean pharmacokinetic data shown in Table 1.

Table 1: Pharmacokinetic Parameters (Median [range]) Following Granisetron Hydrochloride Tablets, USP
 | Peak Plasma Concentration (ng/mL) | Terminal Phase Plasma Half-Life (h) | Volume of Distribution (L/kg) | Total Clearance (L/h/kg)
Cancer Patients 1 mg bid, 7 days (N = 27) | 5.99 [0.63 to 30.9] | N.D. [Not determined after oral administration; following a single intravenous dose of 40 mcg/kg, terminal phase half-life was determined to be 8.95 hours.] | N.D. | 0.52 [0.09 to 7.37]
Volunteers single 1 mg dose (N = 39) | 3.63 [0.27 to 9.14] | 6.23 [0.96 to 19.9] | 3.94 [1.89 to 39.4] | 0.41 [0.11 to 24.6]

Absorption

When granisetron tablets were administered with food, AUC was decreased by 5% and Cmax increased by 30% in non-fasted healthy volunteers who received a single dose of 10 mg.

Distribution

Plasma protein binding is approximately 65% and granisetron distributes freely between plasma and red blood cells.

Metabolism

Granisetron metabolism involves N-demethylation and aromatic ring oxidation followed by conjugation. In vitro liver microsomal studies show that granisetron's major route of metabolism is inhibited by ketoconazole, suggestive of metabolism mediated by the cytochrome P-450 3A subfamily. Animal studies suggest that some of the metabolites may also have 5-HT3 receptor antagonist activity.

Elimination

Clearance is predominantly by hepatic metabolism. In normal volunteers, approximately 11% of the orally administered dose is eliminated unchanged in the urine in 48 hours. The remainder of the dose is excreted as metabolites, 48% in the urine and 38% in the feces.

Subpopulations

Gender

The effects of gender on the pharmacokinetics of granisetron hydrochloride tablets have not been studied. However, after intravenous infusion of granisetron hydrochloride, no difference in mean AUC was found between males and females, although males had a higher Cmax generally.

In elderly and pediatric patients and in patients with renal failure or hepatic impairment, the pharmacokinetics of granisetron was determined following administration of intravenous granisetron.

Elderly

The ranges of the pharmacokinetic parameters in elderly volunteers (mean age 71 years), given a single 40 mcg/kg intravenous dose of granisetron hydrochloride injection, were generally similar to those in younger healthy volunteers; mean values were lower for clearance and longer for half-life in the elderly.

Renal Failure Patients

Total clearance of granisetron was not affected in patients with severe renal failure who received a single 40 mcg/kg intravenous dose of granisetron hydrochloride injection.

Hepatically Impaired Patients

A pharmacokinetic study with intravenous granisetron hydrochloride in patients with hepatic impairment due to neoplastic liver involvement showed that total clearance was approximately halved compared to patients without hepatic impairment. Given the wide variability in pharmacokinetic parameters noted in patients, dosage adjustment in patients with hepatic functional impairment is not necessary.

Pediatric Patients

A pharmacokinetic study in pediatric cancer patients (2 to 16 years of age), given a single 40 mcg/kg intravenous dose of granisetron hydrochloride injection, showed that volume of distribution and total clearance increased with age. No relationship with age was observed for peak plasma concentration or terminal phase plasma half-life. When volume of distribution and total clearance are adjusted for body weight, the pharmacokinetics of granisetron are similar in pediatric and adult cancer patients.

CLINICAL TRIALS

Chemotherapy-Induced Nausea and Vomiting

Granisetron hydrochloride tablets prevent nausea and vomiting associated with initial and repeat courses of emetogenic cancer therapy, as shown by 24 hour efficacy data from studies using both moderately- and highly-emetogenic chemotherapy.

Moderately Emetogenic Chemotherapy

The first trial compared granisetron hydrochloride tablet doses of 0.25 mg to 2 mg twice a day, in 930 cancer patients receiving, principally, cyclophosphamide, carboplatin, and cisplatin (20 mg/m^2 to 50 mg/m^2). Efficacy was based on complete response (i.e., no vomiting, no moderate or severe nausea, no rescue medication), no vomiting, and no nausea. Table 2 summarizes the results of this study.

Table 2: Prevention of Nausea and Vomiting 24 Hours Post-Chemotherapy [Chemotherapy included oral and injectable cyclophosphamide, carboplatin, cisplatin (20 mg/m^2 to 50 mg/m^2), dacarbazine, doxorubicin, epirubicin.]
 | Percentages of Patients Granisetron Hydrochloride Tablet Dose
Efficacy Measures | 0.25 mg twice a day (N = 229) % | 0.5 mg twice a day (N = 235) % | 1 mg twice a day (N = 233) % | 2 mg twice a day (N = 233) %
Complete Response [No vomiting, no moderate or severe nausea, no rescue medication.] | 61 | 70 [Statistically significant (p < 0.01) vs. 0.25 mg bid.] | 81 [Statistically significant (p < 0.01) vs. 0.5 mg bid.] | 72
No Vomiting | 66 | 77 | 88 | 79
No Nausea | 48 | 57 | 63 | 54

Results from a second double-blind, randomized trial evaluating granisetron hydrochloride tablets 2 mg once a day and granisetron hydrochloride tablets 1 mg twice a day were compared to prochlorperazine 10 mg twice a day derived from a historical control. At 24 hours, there was no statistically significant difference in efficacy between the two granisetron hydrochloride tablet regimens. Both regimens were statistically superior to the prochlorperazine control regimen (see Table 3).

Table 3: Prevention of Nausea and Vomiting 24 Hours Post-Chemotherapy [Moderately emetogenic chemotherapeutic agents included cisplatin (20 mg/m^2 to 50 mg/m^2), oral and intravenous cyclophosphamide, carboplatin, dacarbazine, doxorubicin.]
 | Percentages of Patients
Efficacy Measures | Granisetron Hydrochloride Tablets 1 mg twice a day (N = 354) % | Granisetron Hydrochloride Tablets 2 mg once a day (N = 343) % | Prochlorperazine [Historical control from a previous double-blind granisetron hydrochloride trial.] 10 mg twice daily (N = 111) %
Complete Response [No vomiting, no moderate or severe nausea, no rescue medication.] | 69 [Statistically significant (p < 0.05) vs. prochlorperazine historical control.] | 64 | 41
No Vomiting | 82 | 77 | 48
No Nausea | 51 | 53 | 35
Total Control [No vomiting, no nausea, no rescue medication.] | 51 | 50 | 33

Results from a granisetron hydrochloride tablets 2 mg daily alone treatment arm in a third double-blind, randomized trial, were compared to prochlorperazine (PCPZ), 10 mg bid, derived from a historical control. The 24 hour results for granisetron hydrochloride tablets 2 mg daily were statistically superior to PCPZ for all efficacy parameters: complete response (58%), no vomiting (79%), no nausea (51%), total control (49%). The PCPZ rates are shown in Table 3.

Cisplatin-Based Chemotherapy

The first double-blind trial compared granisetron hydrochloride tablets 1 mg bid, relative to placebo (historical control), in 119 cancer patients receiving high-dose cisplatin (mean dose 80 mg/m^2). At 24 hours, granisetron hydrochloride tablets 1 mg bid was significantly (p < 0.001) superior to placebo (historical control) in all efficacy parameters: complete response (52%), no vomiting (56%) and no nausea (45%). The placebo rates were 7%, 14%, and 7%, respectively, for the three efficacy parameters.

Results from a granisetron hydrochloride tablets 2 mg once a day alone treatment arm in a second double-blind, randomized trial, were compared to both granisetron hydrochloride tablets 1 mg twice a day and placebo historical controls. The 24 hour results for granisetron hydrochloride tablets 2 mg once a day were: complete response (44%), no vomiting (58%), no nausea (46%), total control (40%). The efficacy of granisetron hydrochloride tablets 2 mg once a day was comparable to granisetron hydrochloride tablets 1 mg twice a day and statistically superior to placebo. The placebo rates were 7%, 14%, 7%, and 7%, respectively, for the four parameters.

No controlled study comparing granisetron injection with the oral formulation to prevent chemotherapy-induced nausea and vomiting has been performed.

Radiation-Induced Nausea and Vomiting

Total Body Irradiation

In a double-blind randomized study, 18 patients receiving granisetron hydrochloride tablets, 2 mg daily, experienced significantly greater antiemetic protection compared to patients in a historical negative control group who received conventional (non-5-HT3 antagonist) antiemetics. Total body irradiation consisted of 11 fractions of 120 cGy administered over 4 days, with three fractions on each of the first 3 days, and two fractions on the fourth day. Granisetron hydrochloride tablets were given one hour before the first radiation fraction of each day.

Twenty-two percent (22%) of patients treated with granisetron hydrochloride tablets did not experience vomiting or receive rescue antiemetics over the entire 4 day dosing period, compared to 0% of patients in the historical negative control group (p < 0.01).

In addition, patients who received granisetron hydrochloride tablets also experienced significantly fewer emetic episodes during the first day of radiation and over the 4 day treatment period, compared to patients in the historical negative control group. The median time to the first emetic episode was 36 hours for patients who received granisetron hydrochloride tablets.

Fractionated Abdominal Radiation

The efficacy of granisetron hydrochloride tablets, 2 mg daily, was evaluated in a double-blind, placebo-controlled randomized trial of 260 patients. Granisetron hydrochloride tablets were given 1 hour before radiation, composed of up to 20 daily fractions of 180 to 300 cGy each. The exceptions were patients with seminoma or those receiving whole abdomen irradiation who initially received 150 cGy per fraction. Radiation was administered to the upper abdomen with a field size of at least 100 cm^2.

The proportion of patients without emesis and those without nausea for granisetron hydrochloride tablets, compared to placebo, was statistically significant (p < 0.0001) at 24 hours after radiation, irrespective of the radiation dose. Granisetron hydrochloride was superior to placebo in patients receiving up to 10 daily fractions of radiation, but was not superior to placebo in patients receiving 20 fractions.

Patients treated with granisetron hydrochloride tablets (N = 134) had a significantly longer time to the first episode of vomiting (35 days vs. 9 days, p < 0.001) relative to those patients who received placebo (N = 126), and a significantly longer time to the first episode of nausea (11 days vs. 1 day, p < 0.001). Granisetron hydrochloride provided significantly greater protection from nausea and vomiting than placebo.

INDICATIONS AND USAGE

Granisetron hydrochloride tablets USP are indicated for the prevention of:

Nausea and vomiting associated with initial and repeat courses of emetogenic cancer therapy, including high-dose cisplatin.

Nausea and vomiting associated with radiation, including total body irradiation and fractionated abdominal radiation.

CONTRAINDICATIONS

Granisetron hydrochloride tablets are contraindicated in patients with known hypersensitivity to the drug or any of its components.

WARNINGS

Serotonin Syndrome

The development of serotonin syndrome has been reported with 5-HT3 receptor antagonists. Most reports have been associated with concomitant use of serotonergic drugs (e.g., selective serotonin reuptake inhibitors (SSRIs), serotonin and norepinephrine reuptake inhibitors (SNRIs), monoamine oxidase inhibitors, mirtazapine, fentanyl, lithium, tramadol, and intravenous methylene blue). Some of the reported cases were fatal. Serotonin syndrome occurring with overdose of another 5-HT3 receptor antagonist alone has also been reported. The majority of reports of serotonin syndrome related to 5-HT3 receptor antagonist use occurred in a post-anesthesia care unit or an infusion center.

Symptoms associated with serotonin syndrome may include the following combination of signs and symptoms: mental status changes (e.g., agitation, hallucinations, delirium, and coma), autonomic instability (e.g., tachycardia, labile blood pressure, dizziness, diaphoresis, flushing, hyperthermia), neuromuscular symptoms (e.g., tremor, rigidity, myoclonus, hyperreflexia, incoordination), seizures, with or without gastrointestinal symptoms (e.g., nausea, vomiting, diarrhea). Patients should be monitored for the emergence of serotonin syndrome, especially with concomitant use of granisetron and other serotonergic drugs. If symptoms of serotonin syndrome occur, discontinue granisetron and initiate supportive treatment. Patients should be informed of the increased risk of serotonin syndrome, especially if granisetron is used concomitantly with other serotonergic drugs (see Drug Interactions and Patient Counseling Information).

PRECAUTIONS

Granisetron is not a drug that stimulates gastric or intestinal peristalsis. It should not be used instead of nasogastric suction. The use of granisetron in patients following abdominal surgery or in patients with chemotherapy-induced nausea and vomiting may mask a progressive ileus and/or gastric distention.

An adequate QT assessment has not been conducted, but QT prolongation has been reported with granisetron hydrochloride. Therefore, granisetron hydrochloride should be used with caution in patients with pre-existing arrhythmias or cardiac conduction disorders, as this might lead to clinical consequences. Patients with cardiac disease, on cardio-toxic chemotherapy, with concomitant electrolyte abnormalities and/or on concomitant medications that prolong the QT interval are particularly at risk.

Drug Interactions

Granisetron does not induce or inhibit the cytochrome P-450 drug-metabolizing enzyme system in vitro. There have been no definitive drug-drug interaction studies to examine pharmacokinetic or pharmacodynamic interaction with other drugs; however, in humans, granisetron hydrochloride injection has been safely administered with drugs representing benzodiazepines, neuroleptics, and anti-ulcer medications commonly prescribed with antiemetic treatments. Granisetron hydrochloride injection also does not appear to interact with emetogenic cancer chemotherapies. Because granisetron is metabolized by hepatic cytochrome P-450 drug-metabolizing enzymes, inducers or inhibitors of these enzymes may change the clearance and, hence, the half-life of granisetron. No specific interaction studies have been conducted in anesthetized patients. In addition, the activity of the cytochrome P-450 subfamily 3A4 (involved in the metabolism of some of the main narcotic analgesic agents) is not modified by granisetron in vitro.

In in vitro human microsomal studies, ketoconazole inhibited ring oxidation of granisetron. However, the clinical significance of in vivo pharmacokinetic interactions with ketoconazole is not known. In a human pharmacokinetic study, hepatic enzyme induction with phenobarbital resulted in a 25% increase in total plasma clearance of intravenous granisetron. The clinical significance of this change is not known.

QT prolongation has been reported with granisetron hydrochloride. Use of granisetron hydrochloride in patients concurrently treated with drugs known to prolong the QT interval and/or are arrhythmogenic may result in clinical consequences.

Serotonin syndrome (including altered mental status, autonomic instability, and neuromuscular symptoms) has been described following the concomitant use of 5-HT3 receptor antagonists and other serotonergic drugs, including selective serotonin reuptake inhibitors (SSRIs) and serotonin and noradrenaline reuptake inhibitors (SNRIs) (see WARNINGS).

Carcinogenesis, Mutagenesis, Impairment of Fertility

In a 24 month carcinogenicity study, rats were treated orally with granisetron 1, 5 or 50 mg/kg/day (6, 30 or 300 mg/m^2/day). The 50 mg/kg/day dose was reduced to 25 mg/kg/day (150 mg/m^2/day) during week 59 due to toxicity. For a 50 kg person of average height (1.46 m^2 body surface area), these doses represent 4, 20, and 101 times the recommended clinical dose (1.48 mg/m^2, oral) on a body surface area basis. There was a statistically significant increase in the incidence of hepatocellular carcinomas and adenomas in males treated with 5 mg/kg/day (30 mg/m^2/day, 20 times the recommended human dose based on body surface area) and above, and in females treated with 25 mg/kg/day (150 mg/m^2/day, 101 times the recommended human dose based on body surface area). No increase in liver tumors was observed at a dose of 1 mg/kg/day (6 mg/m^2/day, 4 times the recommended human dose based on body surface area) in males and 5 mg/kg/day (30 mg/m^2/day, 20 times the recommended human dose based on body surface area) in females. In a 12 month oral toxicity study, treatment with granisetron 100 mg/kg/day (600 mg/m^2/day, 405 times the recommended human dose based on body surface area) produced hepatocellular adenomas in male and female rats while no such tumors were found in the control rats. A 24 month mouse carcinogenicity study of granisetron did not show a statistically significant increase in tumor incidence, but the study was not conclusive.

Because of the tumor findings in rat studies, granisetron hydrochloride should be prescribed only at the dose and for the indication recommended (see INDICATIONS AND USAGE and DOSAGE AND ADMINISTRATION).

Granisetron was not mutagenic in in vitro Ames test and mouse lymphoma cell forward mutation assay, and in vivo mouse micronucleus test and in vitro and ex vivo rat hepatocyte UDS assays. It, however, produced a significant increase in UDS in HeLa cells in vitro and a significant increased incidence of cells with polyploidy in an in vitro human lymphocyte chromosomal aberration test.

Granisetron at oral doses up to 100 mg/kg/day (600 mg/m^2/day, 405 times the recommended human dose based on body surface area) was found to have no effect on fertility and reproductive performance of male and female rats.

Pregnancy

Teratogenic Effects

Pregnancy Category B

Reproduction studies have been performed in pregnant rats at oral doses up to 125 mg/kg/day (750 mg/m^2/day, 507 times the recommended human dose based on body surface area) and pregnant rabbits at oral doses up to 32 mg/kg/day (378 mg/m^2/day, 255 times the recommended human dose based on body surface area) and have revealed no evidence of impaired fertility or harm to the fetus due to granisetron. There are, however, no adequate and well-controlled studies in pregnant women. Because animal reproduction studies are not always predictive of human response, this drug should be used during pregnancy only if clearly needed.

Nursing Mothers

It is not known whether granisetron is excreted in human milk. Because many drugs are excreted in human milk, caution should be exercised when granisetron hydrochloride is administered to a nursing woman.

Pediatric Use

Safety and effectiveness in pediatric patients have not been established.

Geriatric Use

During clinical trials, 325 patients 65 years of age or older received granisetron hydrochloride tablets; 298 were 65 to 74 years of age, and 27 were 75 years of age or older. Efficacy and safety were maintained with increasing age.

ADVERSE REACTIONS

QT prolongation has been reported with granisetron hydrochloride (see PRECAUTIONS and Drug Interactions).

Chemotherapy-Induced Nausea and Vomiting

Over 3700 patients have received granisetron hydrochloride tablets in clinical trials with emetogenic cancer therapies consisting primarily of cyclophosphamide or cisplatin regimens.

In patients receiving granisetron hydrochloride tablets 1 mg bid for 1, 7 or 14 days, or 2 mg daily for 1 day, adverse experiences reported in more than 5% of the patients with comparator and placebo incidences are listed in Table 4.

Table 4: Principal Adverse Events in Clinical Trials
 | Percent of Patients With Event
 | Granisetron Hydrochloride Tablets [Adverse events were recorded for 7 days when granisetron hydrochloride tablets were given on a single day and for up to 28 days when granisetron hydrochloride tablets were administered for 7 or 14 days.] 1 mg twice a day (N = 978) | Granisetron Hydrochloride Tablets 2 mg once a day (N = 1450) | Comparator [Metoclopramide/dexamethasone; phenothiazines/dexamethasone; dexamethasone alone; prochlorperazine.] (N = 599) | Placebo (N = 185)
Headache [Usually mild to moderate in severity.] | 21% | 20% | 13% | 12%
Constipation | 18% | 14% | 16% | 8%
Asthenia | 14% | 18% | 10% | 4%
Diarrhea | 8% | 9% | 10% | 4%
Abdominal Pain | 6% | 4% | 6% | 3%
Dyspepsia | 4% | 6% | 5% | 4%

Other adverse events reported in clinical trials were:

Gastrointestinal: In single-day dosing studies in which adverse events were collected for 7 days, nausea (20%) and vomiting (12%) were recorded as adverse events after the 24 hour efficacy assessment period.

Hepatic: In comparative trials, elevation of AST and ALT (> 2 times the upper limit of normal) following the administration of granisetron hydrochloride tablets occurred in 5% and 6% of patients, respectively. These frequencies were not significantly different from those seen with comparators (AST: 2%; ALT: 9%).

Cardiovascular: Hypertension (1%); hypotension, angina pectoris, atrial fibrillation, and syncope have been observed rarely.

Central Nervous System: Dizziness (5%), insomnia (5%), anxiety (2%), somnolence (1%). One case compatible with, but not diagnostic of, extrapyramidal symptoms has been reported in a patient treated with granisetron hydrochloride tablets.

Hypersensitivity: Rare cases of hypersensitivity reactions, sometimes severe (e.g., anaphylaxis, shortness of breath, hypotension, urticaria) have been reported.

Other: Fever (5%). Events often associated with chemotherapy also have been reported: leukopenia (9%), decreased appetite (6%), anemia (4%), alopecia (3%), thrombocytopenia (2%).

Over 5000 patients have received injectable granisetron hydrochloride in clinical trials.

Table 5 gives the comparative frequencies of the five commonly reported adverse events (≥ 3%) in patients receiving granisetron hydrochloride injection, 40 mcg/kg, in single-day chemotherapy trials. These patients received chemotherapy, primarily cisplatin, and intravenous fluids during the 24 hour period following granisetron hydrochloride injection administration.

Table 5: Principal Adverse Events in Clinical Trials—Single-Day Chemotherapy
 | Percent of Patients with Event
 | Granisetron Hydrochloride Injection [Adverse events were generally recorded over 7 days post-granisetron hydrochloride injection administration.] 40 mcg/kg (N = 1268) | Comparator [Metoclopramide/dexamethasone and phenothiazines/dexamethasone.] (N = 422)
Headache | 14% | 6%
Asthenia | 5% | 6%
Somnolence | 4% | 15%
Diarrhea | 4% | 6%
Constipation | 3% | 3%

In the absence of a placebo group, there is uncertainty as to how many of these events should be attributed to granisetron hydrochloride, except for headache, which was clearly more frequent than in comparison groups.

Radiation-Induced Nausea and Vomiting

In controlled clinical trials, the adverse events reported by patients receiving granisetron hydrochloride tablets and concurrent radiation were similar to those reported by patients receiving granisetron hydrochloride tablets prior to chemotherapy. The most frequently reported adverse events were diarrhea, asthenia, and constipation. Headache, however, was less prevalent in this patient population.

Postmarketing Experience

QT prolongation has been reported with granisetron hydrochloride (see PRECAUTIONS and Drug Interactions).

OVERDOSAGE

There is no specific treatment for granisetron hydrochloride overdosage. In case of overdosage, symptomatic treatment should be given. Overdosage of up to 38.5 mg of granisetron hydrochloride injection has been reported without symptoms or only the occurrence of a slight headache.

DOSAGE AND ADMINISTRATION

Emetogenic Chemotherapy

The recommended adult dosage of oral granisetron hydrochloride tablets USP is 2 mg once daily or 1 mg twice daily. In the 2 mg once-daily regimen, two 1 mg tablets are given up to 1 hour before chemotherapy. In the 1 mg twice-daily regimen, the first 1 mg tablet is given up to 1 hour before chemotherapy, and the second tablet, 12 hours after the first. Either regimen is administered only on the day(s) chemotherapy is given. Continued treatment, while not on chemotherapy, has not been found to be useful.

Use in the Elderly, Renal Failure Patients or Hepatically Impaired Patients

No dosage adjustment is recommended (see CLINICAL PHARMACOLOGY, Pharmacokinetics).

Pediatric Use

Safety and effectiveness in pediatric patients have not been established.

Radiation (Either Total Body Irradiation or Fractionated Abdominal Radiation)

The recommended adult dosage of oral granisetron hydrochloride tablets USP is 2 mg once daily.

Two 1 mg tablets are taken within 1 hour of radiation.

Pediatric Use

Safety and effectiveness in pediatric patients have not been established.

Use in the Elderly

No dosage adjustment is recommended.

HOW SUPPLIED

Granisetron hydrochloride tablets USP are available as:

White colored, triangular shaped, biconvex, film-coated tablets with debossing of '1GN' on one side and plain surface on the other side.

Granisetron HCl tablets, USP are available as 20 Unit Dose tablets and 2's pack.
NDC 51991-735-20-20'S Pack
NDC 51991-735-32 - 2'S Pack

Storage

Store between 20° and 25°C (68° and 77°F) [see USP Controlled Room Temperature]. Keep container closed tightly.

Protect from light. Retain in carton until time of use.

PATIENT COUNSELING INFORMATION

Advise patients of the possibility of serotonin syndrome with concomitant use of granisetron and another serotonergic agent such as medications to treat depression and migraines. Advise patients to seek immediate medical attention if the following symptoms occur: changes in mental status, autonomic instability, neuromuscular symptoms with or without gastrointestinal symptoms.

Manufactured by:
NATCO PHARMA LIMITED
Kothur- 509 228,
India.

Distributed by:
Breckenridge Pharmaceutical, Inc.
Berkeley Heights, NJ 07922

01/2024

40500409

PRINCIPAL DISPLAY PANEL - 1 mg Tablet Blister Pack Carton

NDC 51991-735-32

Granisetron Hydrochloride
Tablets, USP

1 mg* per tablet

This unit-dose package is not child-resistant.

breckenridge
A Towa
Company

Rx Only
Contains two
1 mg tablets